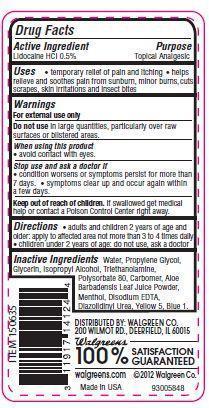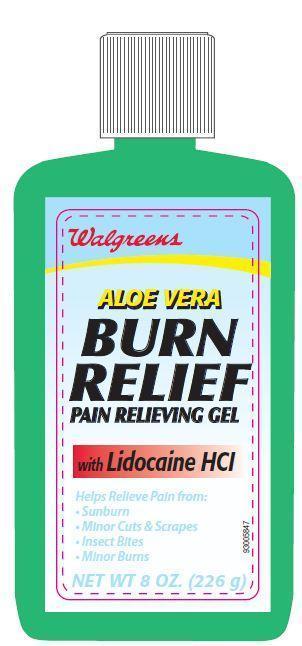 DRUG LABEL: Walgreens Aloe Vera Burn Relief 
NDC: 0363-4000 | Form: GEL
Manufacturer: WALGREEN CO.
Category: otc | Type: HUMAN OTC DRUG LABEL
Date: 20121204

ACTIVE INGREDIENTS: LIDOCAINE HYDROCHLORIDE 0.5 g/100 g
INACTIVE INGREDIENTS: WATER; TROLAMINE; ISOPROPYL ALCOHOL; EDETATE DISODIUM; ALOE VERA LEAF; PROPYLENE GLYCOL; GLYCERIN; POLYSORBATE 80; DIAZOLIDINYL UREA; MENTHOL

Drug Facts

Active Ingredient

Lidocaine HCl 0.50%

Purpose

Topical Analgesic

Uses

- temporary pain relief
- helps relieve and soothes pain from sunburn, minor burns, cuts, scrapes, skin irritations and insect bites.

Warnings

For external use only

Do not use in large quantities, particularly over raw surfaces or blistered areas.

When using this product

- avoid contact with eyes.

stop use and ask a doctor if

- conditions worsens or symptoms persists for more than 7 days.
- Symptoms clear up and occur again within a few days.

Keep out of reach of children.

If swallowed get medical help or contact a Poison Control Center right away.

Directions

- adults and children 2 years of age and older.apply to affected area not more than 3 to 4 times daily
- children under 2 years of age: do not use, ask a doctor.

Inactive Ingredients

Water, Propylene Glycol, Glycerin, Isopropyl Alcohol, Triethanolamine, Polysorbate 80, Carbomer, Aloe Barbadensis Leaf Juice Powder, Menthol, Disodium EDTA, Diazolidinyl Urea, Yellow 5, Blue 1.

Principal Display Panel

walgreens
ALOE VERA
BURN
RELIEF
PAIN RELIEVING GEL
with LIDOCAINE HCLHelps Relieve Pain from:
Sunburn
Minor Cuts and scrapes
Insect Bites
Minor Burns
NET WT 8 OZ. (226 g)